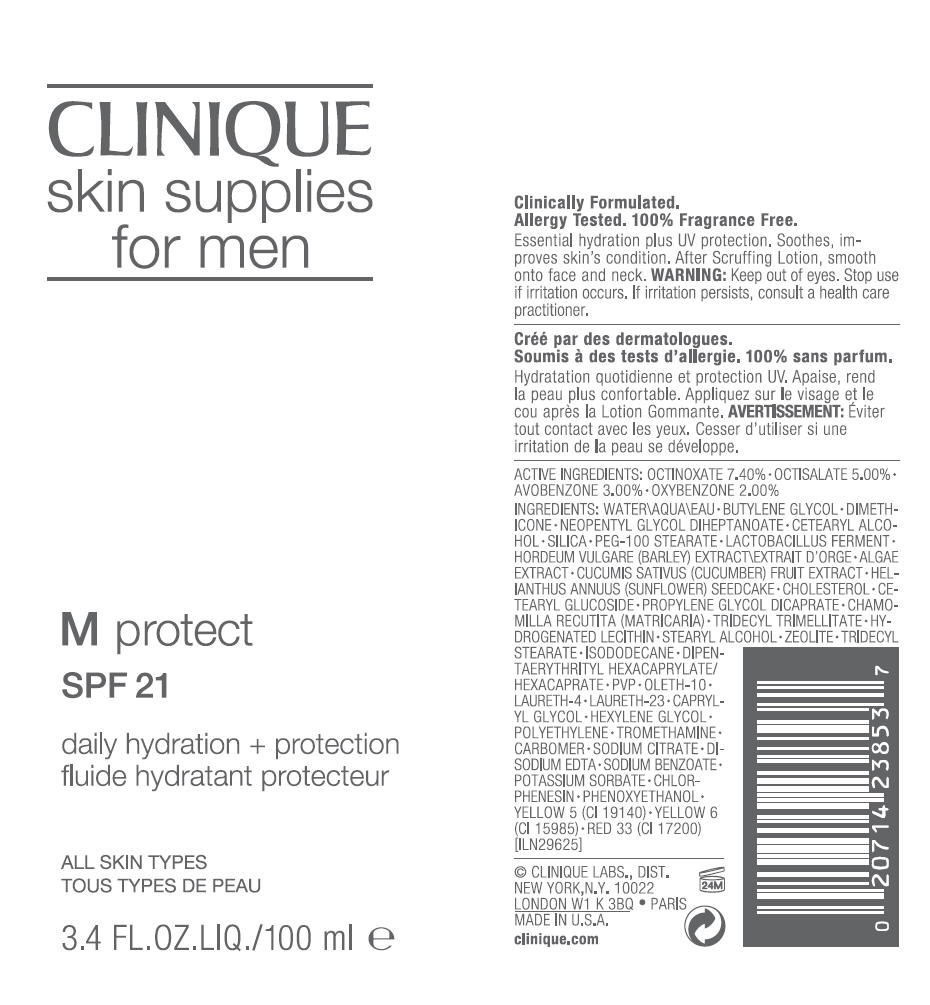 DRUG LABEL: CLINIQUE 
NDC: 49527-886 | Form: LOTION
Manufacturer: CLINIQUE  LABORATORIES INC.
Category: otc | Type: HUMAN OTC DRUG LABEL
Date: 20111201

ACTIVE INGREDIENTS: octinoxate 7.4 mL/100 mL; octisalate 5 mL/100 mL; avobenzone 3 mL/100 mL; oxybenzone 2 mL/100 mL
INACTIVE INGREDIENTS: water; butylene glycol; dimethicone; neopentyl glycol diheptanoate; cetostearyl alcohol; silicon dioxide; peg-100 stearate; barley; cucumber; helianthus annuus seedcake; cholesterol; cetearyl glucoside; propylene glycol dicaprate; matricaria recutita; tridecyl trimellitate; stearyl alcohol; tridecyl stearate; isododecane; dipentaerythrityl hexacaprylate/hexacaprate; oleth-10; laureth-4; laureth-23; caprylyl glycol; hexylene glycol; high density polyethylene; tromethamine; sodium citrate; edetate disodium; sodium benzoate; potassium sorbate; chlorphenesin; phenoxyethanol; fd&c yellow no. 5; fd&c yellow no. 6; d&c red no. 33

CLINIQUE
skin supplies
for men

WARNING

Keep out of eyes.

Stop use if irritation occurs. If irritation persists, consult a health care practitioner.

ACTIVE INGREDIENTS

OCTINOXATE 7.40% • OCTISALATE 5.00% • AVOBENZONE 3.00% • OXYBENZONE 2.00%

INGREDIENTS

WATER • BUTYLENE GLYCOL • DIMETHICONE • NEOPENTYL GLYCOL DIHEPTANOATE • CETEARYL ALCOHOL • SILICA • PEG-100 STEARATE • LACTOBACILLUS FERMENT • HORDEUM VULGARE (BARLEY) EXTRACT • ALGAE EXTRACT • CUCUMIS SATIVUS (CUCUMBER) FRUIT EXTRACT • HELIANTHUS ANNUUS (SUNFLOWER) SEEDCAKE • CHOLESTEROL • CETEARYL GLUCOSIDE • PROPYLENE GLYCOL DICAPRATE • CHAMOMILLA RECUTITA (MATRICARIA) • TRIDECYL TRIMELLITATE • HYDROGENATED LECITHIN • STEARYL ALCOHOL • ZEOLITE • TRIDECYL STEARATE • ISODODECANE • DIPENTAERYTHRITYL HEXACAPRYLATE/HEXACAPRATE • PVP • OLETH-10 • LAURETH-4 • LAURETH-23 • CAPRYLYL GLYCOL • HEXYLENE GLYCOL • POLYETHYLENE • TROMETHAMINE • CARBOMER • SODIUM CITRATE • DISODIUM EDTA • SODIUM BENZOATE • POTASSIUM SORBATE • CHLORPHENESIN • PHENOXYETHANOL • YELLOW 5 (CI 19140) • YELLOW 6 (CI 15985) • RED 33 (CI 17200) [ILN29625]

© CLINIQUE LABS., DIST.
NEW YORK,N.Y. 10022

PRINCIPAL DISPLAY PANEL - 100 ml Bottle Carton

CLINIQUE
skin supplies
for men

M protect
SPF 21

daily hydration + protection

ALL SKIN TYPES

3.4 FL.OZ.LIQ./100 ml e